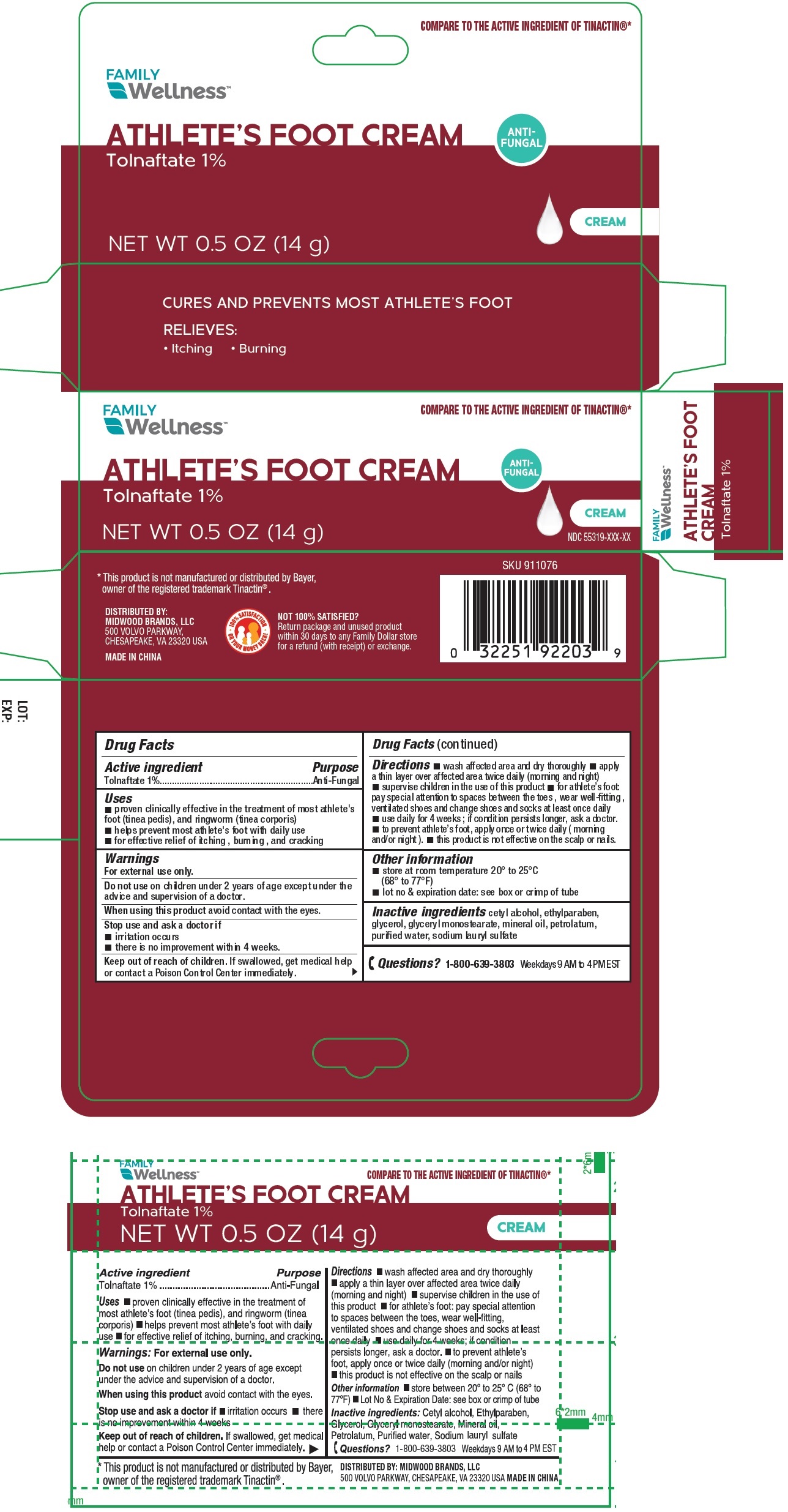 DRUG LABEL: Family Wellness Athletes Foot Tolnaftate 1 Cream
NDC: 55319-991 | Form: CREAM
Manufacturer: Family Dollar Stores, Inc
Category: otc | Type: HUMAN OTC DRUG LABEL
Date: 20250225

ACTIVE INGREDIENTS: TOLNAFTATE 10 mg/1 g
INACTIVE INGREDIENTS: CETYL ALCOHOL; ETHYLPARABEN; GLYCERIN; GLYCERYL MONOSTEARATE; MINERAL OIL; PETROLATUM; WATER; SODIUM LAURYL SULFATE

Family Wellness Athletes Foot Tolnaftate 1% Cream

Active ingredient

Tolnaftate 1%

Purpose

Anti-Funga

Uses

- proven clinically effective in the treatment of most athlete's foot (tinea pedis), and ringworm (tinea corporis)
- helps prevent most athlete's foot with daily use
- for effective relief of itching , burning , and cracking

Warnings

For external use only.

Do not use

on children under 2 years of age except under the advice and supervision of a doctor.

When using this product

avoid contact with the eyes.

Stop use and ask a doctor if

- irritation occurs.
- there is no improvement within 4 weeks.

Keep out of reach of children.

If swallowed, get medical help or contact a Poison Control Center immediately.

Directions

- wash the affected area and dry thoroughly
- apply a thin layer over affected area twice daily (morning and night)
- supervise children in the use of this product.
- for athlete's foot, pay special attention to the spaces between the toes; wear well-fitting ventilated shoes, and change shoes and socks at least once daily.
- use daily for 4 weeks; if condition persists longer, ask a doctor.
- to prevent athlete's foot, apply once or twice daily (morning and/or night).
- this product is not effective on the scalp or nails.

Other info rmation

- store at room temperature 20°-25°C (68°-77°F).
- lot no & expiration date: see box or crimp of tube

Inactive ingredients

cetyl alcohol, ethylparaben, glycerol, glyceryl monostearate, mineral oil, petrolatum, purified water, sodium lauryl sulfate

Questions?

1-800-639-3803Weekdays 9 AM to 4 PM EST